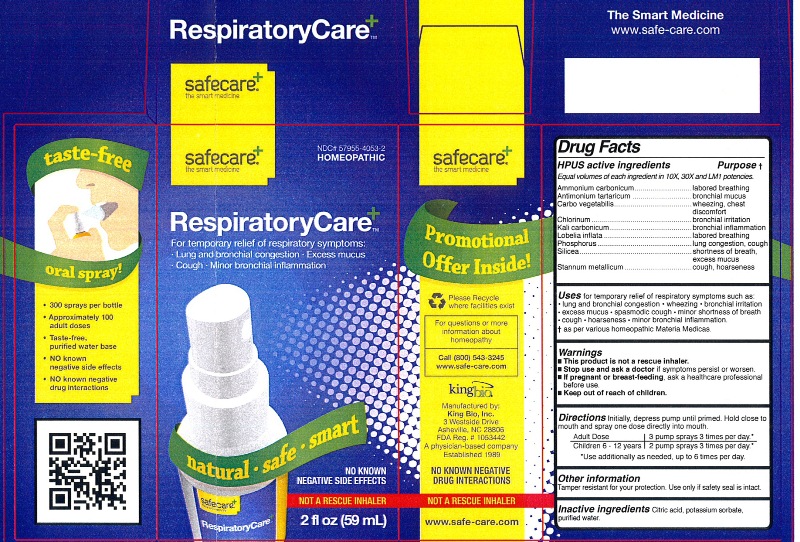 DRUG LABEL: RespiratoryCare
NDC: 57955-4053 | Form: LIQUID
Manufacturer: King Bio Inc
Category: homeopathic | Type: HUMAN OTC DRUG LABEL
Date: 20120605

ACTIVE INGREDIENTS: AMMONIUM CARBONATE 10 [hp_X]/59 mL; ANTIMONY POTASSIUM TARTRATE 10 [hp_X]/59 mL; ACTIVATED CHARCOAL 10 [hp_X]/59 mL; CHLORINE 10 [hp_X]/59 mL; POTASSIUM CARBONATE 10 [hp_X]/59 mL; LOBELIA INFLATA 10 [hp_X]/59 mL; PHOSPHORUS 10 [hp_X]/59 mL; SILICON DIOXIDE 10 [hp_X]/59 mL; TIN 10 [hp_X]/59 mL
INACTIVE INGREDIENTS: WATER; POTASSIUM SORBATE; CITRIC ACID MONOHYDRATE

RespiratoryCare

Active Ingredients

HPUS active ingredients

Equal volumes of each ingredient in 10X, 30X and LM1 potencies.

Ammonium carbonicum, Antimonium tartaricum, Carbo vegetabilis, Chlorinum, Kali carbonicum, Lobelia inflata, Phosphorus, Silicea, and Stannum metallicum.

Reference image respiratorycare.jpg

Inactive Ingredients

Citric acid, potassium sorbate, and purified water.

Reference image respiratorycare.jpg

Directions

Initially, depress pump until primed. Hold close to mouth and spray one dose directly into mouth.

Adult Dose: 3 pump sprays 3 times per day.

Children 6 -12 years: 2 pump sprays 3 times per day.

Use additionally as needed, up to 6 times per day.

Reference image respiratorycare.jpg

Purpose

HPUS active ingredients Purpose

Equal volumes of each ingredient in 10X, 30X and LM1

Ammonium carbonicum....................................................labored breathing

Antimonium tartaricum.....................................................bronchial mucus

Carbo vegetabilis.............................................................wheezing, chest discomfort

Chlorinum.......................................................................bronchial irritation

Kali carbonicum..............................................................bronchial inflammation

Lobelia inflata..................................................................labored breathing

Phosphorus....................................................................lung congestion, cough

Silicea............................................................................shortness of breath, excess mucus

Stannum metallicum........................................................cough, hoarseness

Reference image respiratorycare.jpg

Warnings

- This product is not a rescue inhaler.
- Stop use and ask a doctor if symptoms persist or worsen.
- If pregnant or breast-feeding, ask a healthcare professional before use.
- Keep out of reach of children.

Other information: Tamper resistant for your protection. Use only if safety seal is intact.
Reference image respiratorycare.jpg

Keep out of reach of children

Indications and Usage

Uses for temporary relief of respiratory symptoms such as:

- lung and bronchial congestion
- wheezing
- bronchial irritation
- excess mucus
- spasmodic cough
- minor shortness of breath
- cough
- hoarseness
- minor bronchial inflammation

as per various homeopathic Materia Medicas.
Reference image respiratorycare.jpg

PACKAGE LABEL

King Bio, Inc

3 Westside Drive

Asheville, NC 28806

Questions? Call 800.543.3245

www.safe-care.com